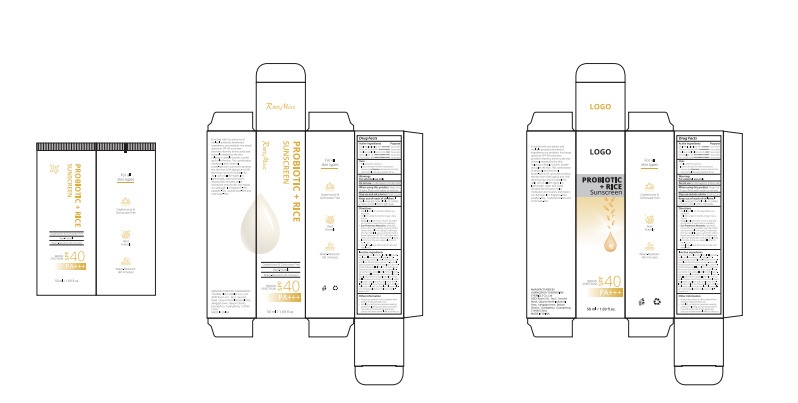 DRUG LABEL: PROBIOTIC RICE Sunscreen
NDC: 84558-006 | Form: CREAM
Manufacturer: GUANGZHOU YUSONG FINE CHEMICLS Co., Ltd
Category: otc | Type: HUMAN OTC DRUG LABEL
Date: 20250208

ACTIVE INGREDIENTS: TITANIUM DIOXIDE 4 g/100 mL; PHENYLBENZIMIDAZOLE SULFONIC ACID 3.2 g/100 mL; HOMOSALATE 1 g/100 mL; ZINC OXIDE 0.6 g/100 mL; ETHYLHEXYL SALICYLATE 5 g/100 mL
INACTIVE INGREDIENTS: TRIETHOXYCAPRYLYLSILANE; LACTOBACILLUS; CLOVE; SODIUM HYDROXIDE; AQUA; DIMETHICONE; GLYCERIN; BUTYLENE GLYCOL; ISOHEXADECANE; ISONONYL ISONONANOATE; CETYL PEG/PPG-10/1 DIMETHICONE (HLB 4); NIACINAMIDE; SILICA; PEG-10 DIMETHICONE (200 CST); SODIUM CHLORIDE; DISTEARDIMONIUM HECTORITE; 1,2-HEXANEDIOL; HYDROXYACETOPHENONE; SORBITAN SESQUIOLEATE; HYALURONIC ACID; CAPRYLHYDROXAMIC ACID; RICE AMINO ACIDS; SODIUM HYALURONATE; ALPHA-TOCOPHEROL ACETATE; XANTHAN GUM; PHENOXYETHANOL; SODIUM S-(2-HYDROXY-3-(3-(TRIHYDROXYSILYL)PROPOXY)PROPYL) SULFUROTHIOATE; HYDROLYZED CASEIN (ENZYMATIC; 1000 MW); PROPANEDIOL; SODIUM ACETYLATED HYALURONATE; PEG-9 DIGLYCIDYL ETHER/SODIUM HYALURONATE CROSSPOLYMER; ORYZA SATIVA (RICE) GERM POWDER; ALUMINUM HYDROXIDE

84558-006

Active Ingredient(s)

Ethylhexy| Salicylate 5%
Titanium Dioxide 4%
Phenylbenzimidazole Sulfonic Acid 3.2%
Homosalate 1%
Zinc Oxide 0.6%

Purpose

Sunscreen .

Use

1.helps prevent sunburn
2.If used as directed with other sun protection measures (see Directions), decreases the risk of skin
cancer and early skin aging caused by the sun

Warnings

For external use only

Do not use on damaged or broken skin

When using this product keep out of eyes. Rinse with water to remove

Stop use and ask a doctor if rash occurs

Keep out of reach of children. If swallowed, get medical help or contact a Poison Control C enter right away

Directions

● Apply liberally 15 minutes before sun exposure.
● Children under 6 months of age :Ask a doctor.
● Reapply at least every 2 hours, and after 40 minutes of swimming or sweating.
●Sun Protection Measures. Spending time in the sun increases your risk of skin cancer and early skin aging. To decrease
this risk, regularly use a sunscreen with a Broad Spectrum SPF of 15 or higher and other sun protection measures including:
●limit time in the sun, especially from10. a.m.-2 p.m.
●wear long-sleeve shirts, pants, hats, and sunglasses

Other information

● Protect the product in this container from excessive heat and direct sun.
●Sun alert: Limiting sun exposure, wearing protective clothing, and using sunscreens may reduce the risks of skin aging, skin
cancer, and other harmful effects of the sun.

Inactive ingredients

Aqua, Dimethicone, Glycerin, Butylene Glycol, Isohexadec- ane, Isononyl lsononanoate, Cetyl Peg/Ppg-10/1 Di-
methicone, Niacinamide, Slica, Peg-10 Dimethicone, Sodi-um Chloride, Disteardimonium Hectorite, 1,2-Hexanediol,
Hydroxyacetophenone, Sorbitan Sesquioleate, Sodium Hy-droxide, Triethoxyapysilane, Aluminum Hydroxide, Rice
Amino Acids, Oryza Sativa (Rice) Extract, Tocopheryl Ace-tate, Xanthan Gum, L actobacillus/Milk Ferment Filtrate,

Fra-grance, Lactobailus/Soybean Extract Ferment Filtrate, Lac-tobaillus/Rice Ferment, Lactobailus/Rye Flour Ferment,
Bacillus/Soybean Ferment Extract, Phenoxyethanol, Sodium Hyaluronate Crosspolymer, Sodium Hyaluronate, Hydro-
lyzed Sodium Hyaluronate Propanediol, Sodium Acetylated Hyaluronate, Hyaluronic Acid, Hydrolyzed Glycosaminogl-
cans, Hydroxypropytimonium Hyaluronate, Caprylhy-droxamic Acid